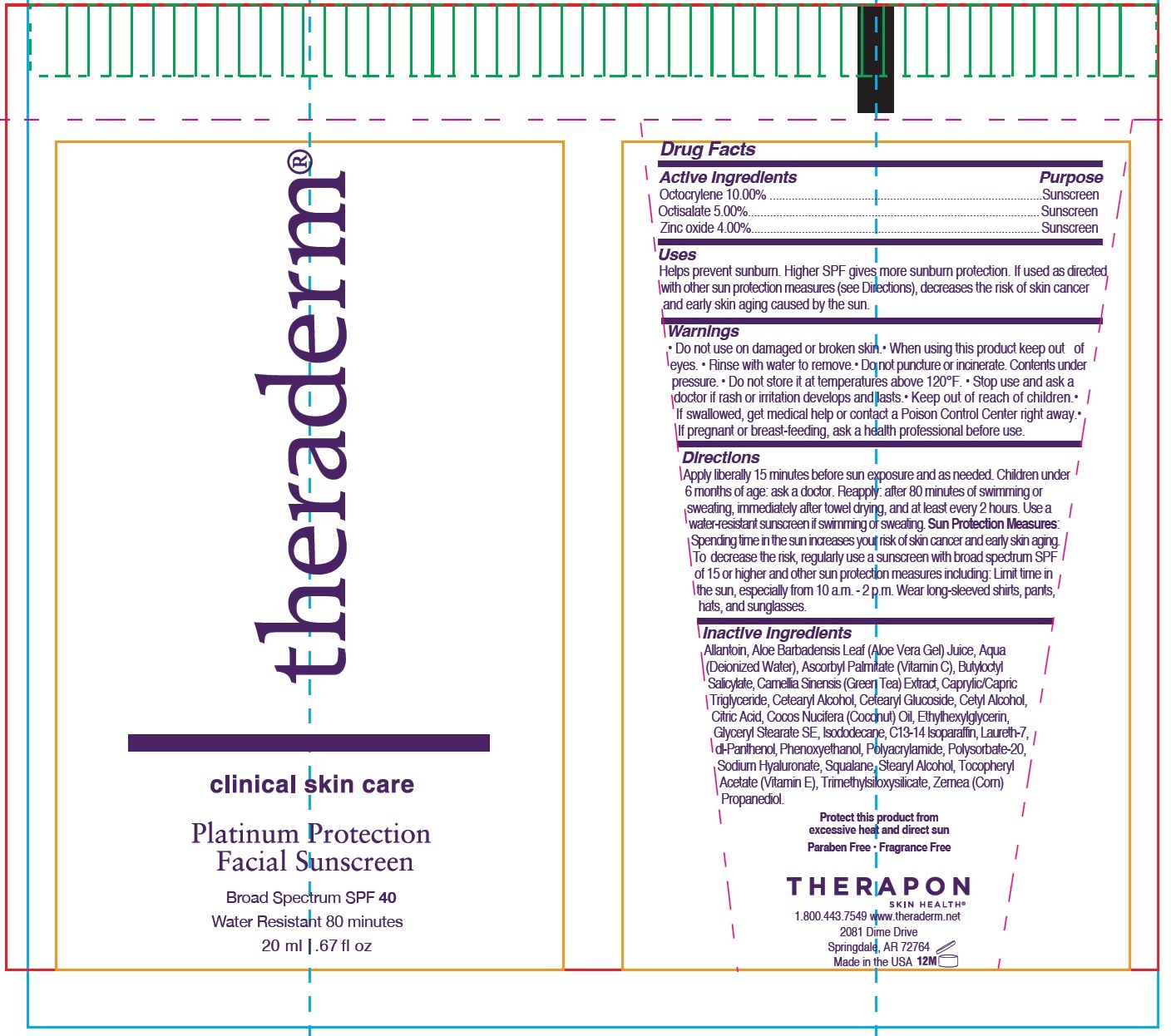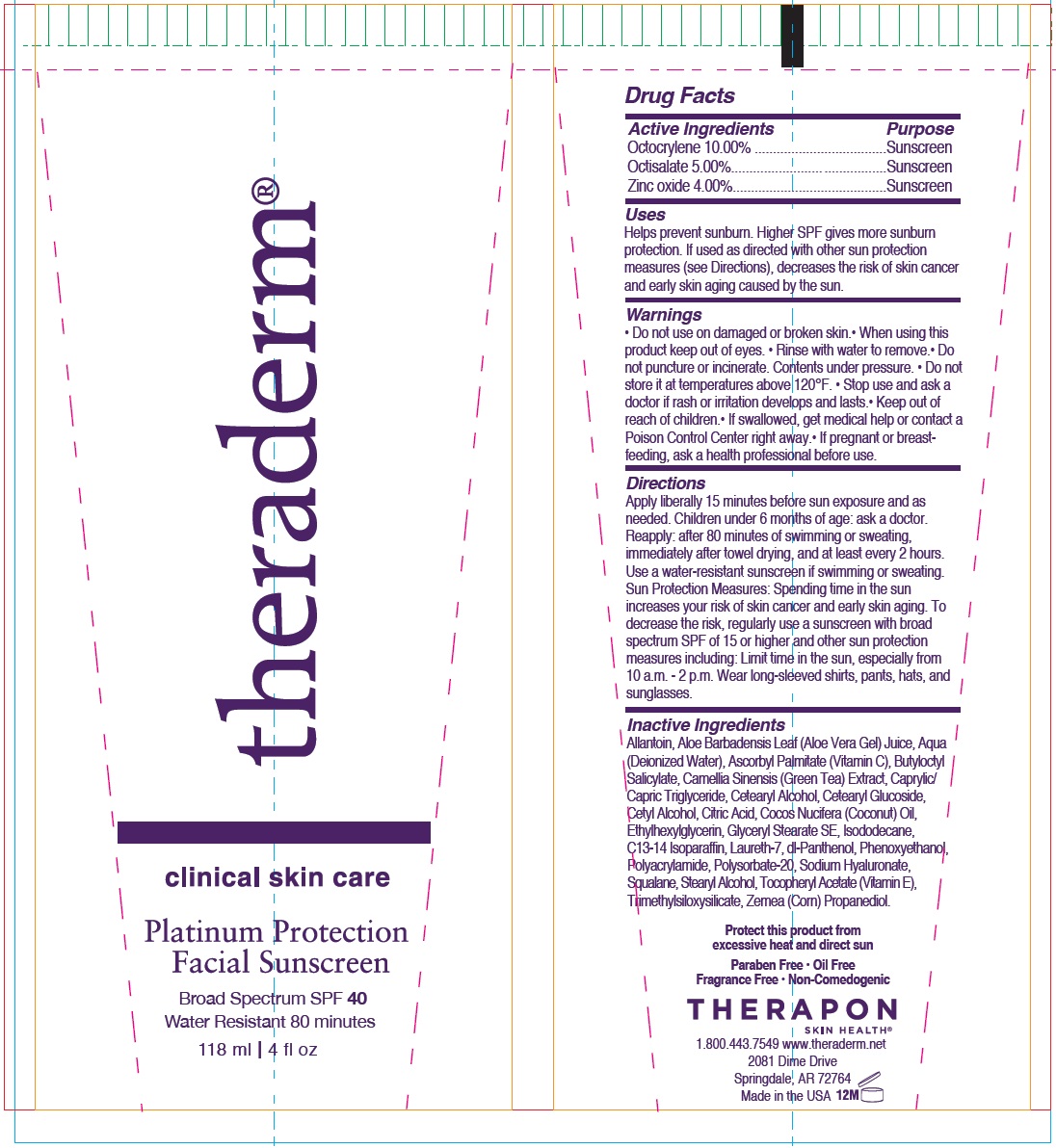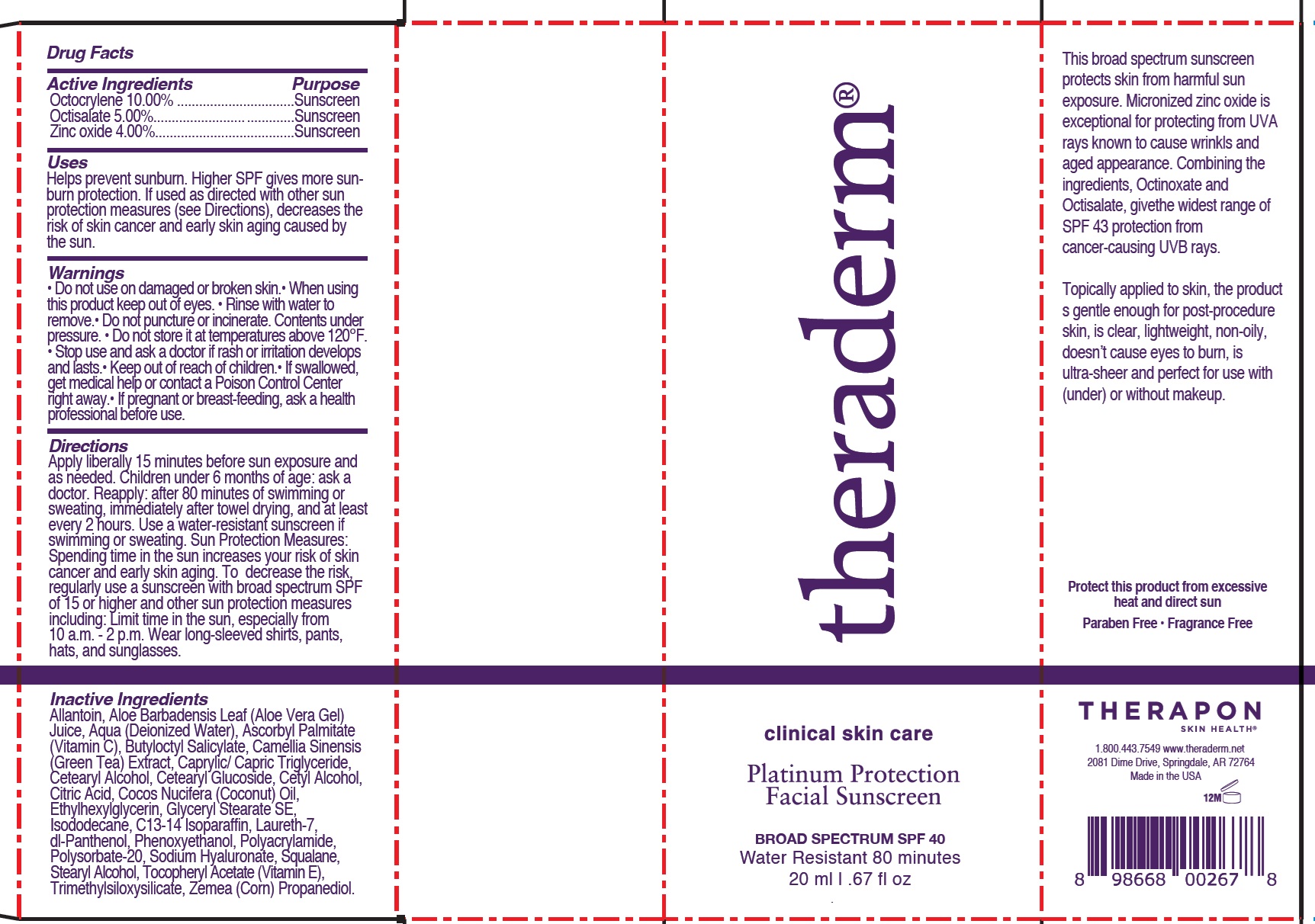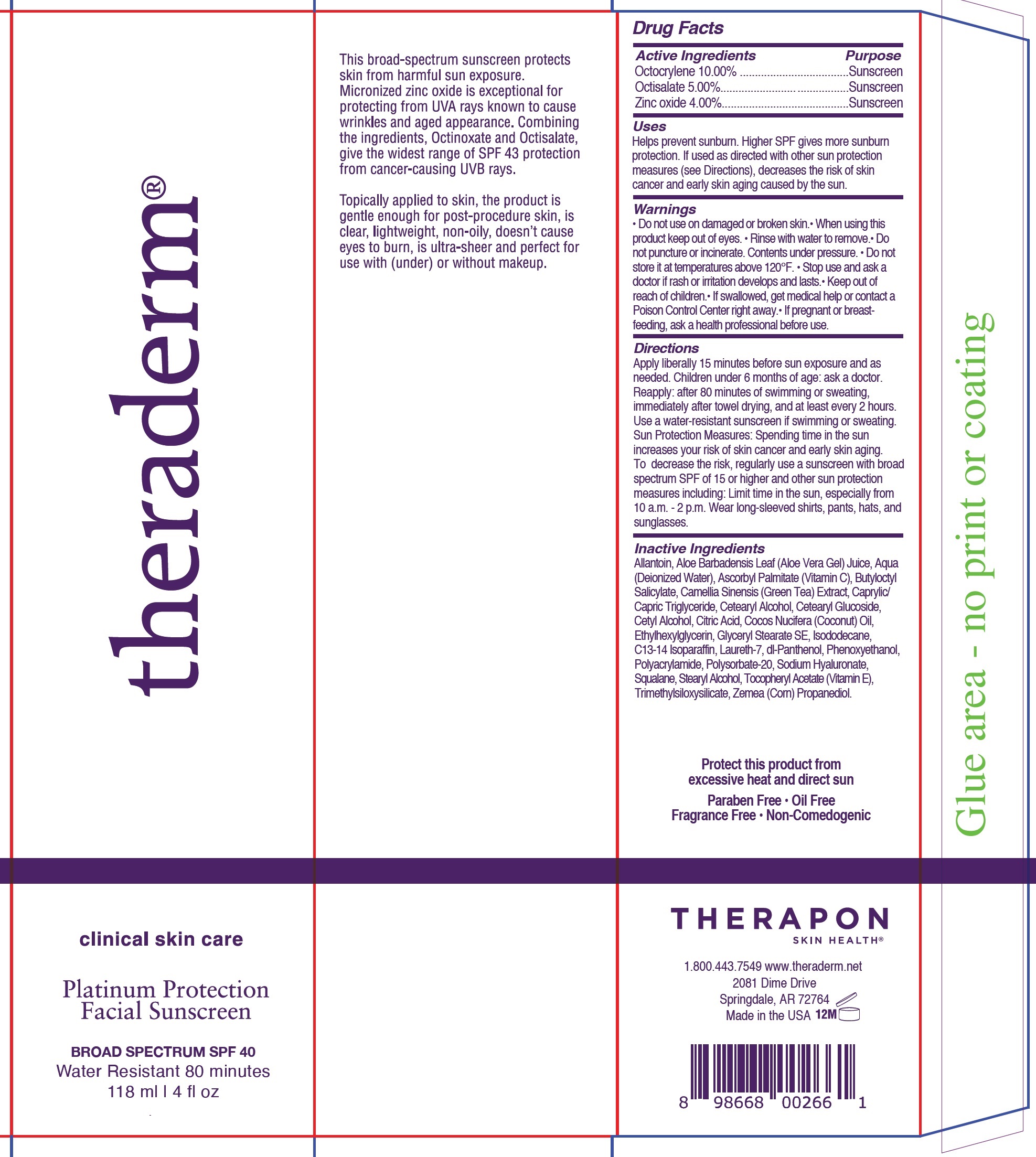 DRUG LABEL: Theraderm Platinum Protection Facial Sunscreen SPF 40
NDC: 66428-567 | Form: LOTION
Manufacturer: Therapon Inc
Category: otc | Type: HUMAN OTC DRUG LABEL
Date: 20241119

ACTIVE INGREDIENTS: OCTOCRYLENE 100 mg/1 mL; OCTISALATE 50 mg/1 mL; ZINC OXIDE 40 mg/1 mL
INACTIVE INGREDIENTS: ALLANTOIN; ALOE VERA LEAF; WATER; ASCORBYL PALMITATE; BUTYLOCTYL SALICYLATE; GREEN TEA LEAF; MEDIUM-CHAIN TRIGLYCERIDES; CETOSTEARYL ALCOHOL; CETEARYL GLUCOSIDE; CETYL ALCOHOL; CITRIC ACID MONOHYDRATE; COCONUT OIL; ETHYLHEXYLGLYCERIN; GLYCERYL STEARATE SE; ISODODECANE; C13-14 ISOPARAFFIN; LAURETH-7; PANTHENOL; PHENOXYETHANOL; POLYSORBATE 20; SODIUM HYALURONATE; SQUALANE; STEARYL ALCOHOL; .ALPHA.-TOCOPHEROL ACETATE; CORN

Theraderm Platinum Protection Facial Sunscreen SPF 40

Active Ingredients

Octocrylene 10.00%

Octisalate 5.00%

Zinc oxide 4.00%

Purpose

Sunscreen

Uses

Helps prevent sunburn. Higher SPF gives more sunburn protection. If used as directed with other sun protection measures (see Directions), decreases the risk of skin cancer and early skin aging caused by the sun.

Warnings

Do not use

- on damaged or broken skin.

When using this product

- keep out of eyes. • Rinse with water to remove.• Do not puncture or incinerate. Contents underpressure. • Do not store it at temperatures above 120°F.

Stop use and ask a doctor

- if rash or irritation develops and lasts.

Keep out of reach of children.

• If swallowed, get medical help or contact a Poison Control Center right away.

If pregnant or breast-feeding,

ask a health professional before use.

Directions

Apply liberally 15 minutes before sun exposure and as needed. Children under 6 months of age: ask a doctor. Reapply: after 80 minutes of swimming or sweating, immediately after towel drying, and at least every 2 hours. Use a water-resistant sunscreen if swimming or sweating. Sun Protection Measures: Spending time in the sun increases your risk of skin cancer and early skin aging. To decrease the risk, regularly use a sunscreen with broad spectrum SPF of 15 or higher and other sun protection measures including: Limit time in the sun, especially from 10 a.m. - 2 p.m. Wear long-sleeved shirts, pants, hats, and sunglasses.

Inactive Ingredients

Allantoin, Aloe Barbadensis Leaf (Aloe Vera Gel) Juice, Aqua (Deionized Water), Ascorbyl Palmitate (Vitamin C), Butyloctyl Salicylate, Camellia Sinensis (Green Tea) Extract, Caprylic/ Capric Triglyceride, Cetearyl Alcohol, Cetearyl Glucoside, Cetyl Alcohol, Citric Acid, Cocos Nucifera (Coconut) Oil, Ethylhexylglycerin, Glyceryl Stearate SE, Isododecane, C13-14 Isoparaffin, Laureth-7, dl-Panthenol, Phenoxyethanol, Polyacrylamide, Polysorbate-20, Sodium Hyaluronate, Squalane, Stearyl Alcohol, Tocopheryl Acetate (Vitamin E), Trimethylsiloxysilicate, Zemea (Corn) Propanediol.